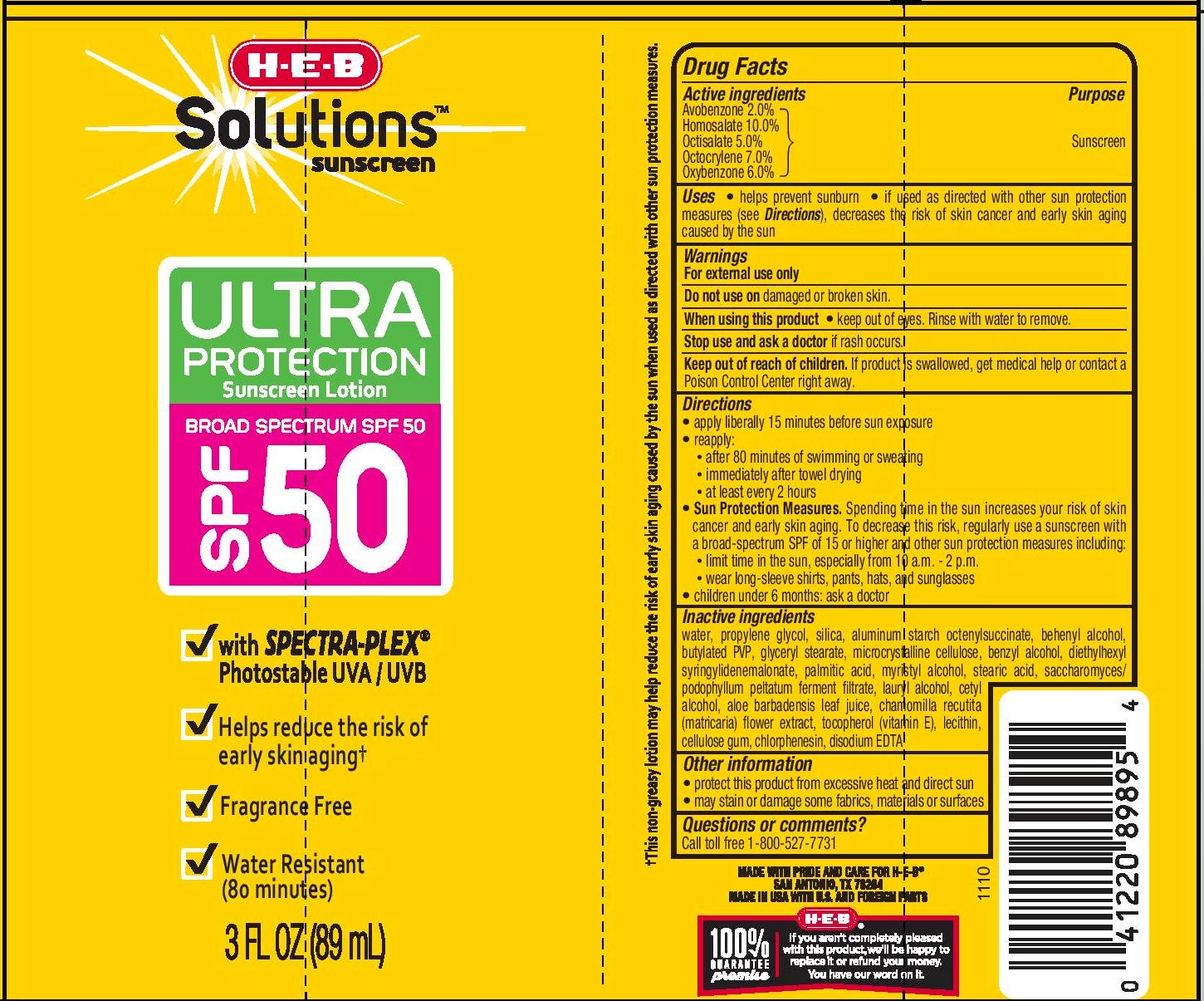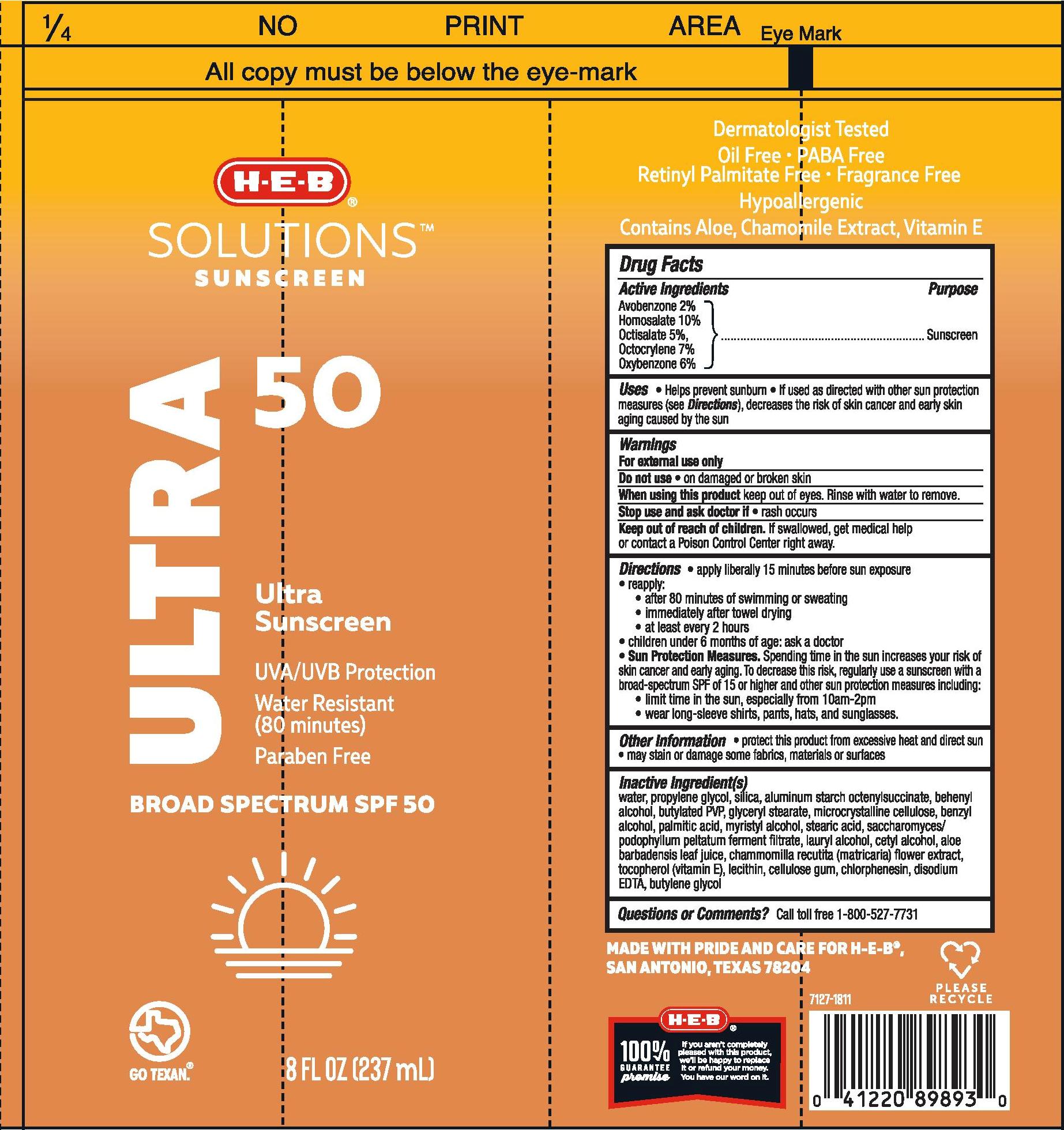 DRUG LABEL: H.E.B
NDC: 37808-956 | Form: LOTION
Manufacturer: H.E.B
Category: otc | Type: HUMAN OTC DRUG LABEL
Date: 20241015

ACTIVE INGREDIENTS: AVOBENZONE 20 mg/1 mL; HOMOSALATE 100 mg/1 mL; OCTISALATE 50 mg/1 mL; OCTOCRYLENE 70 mg/1 mL; OXYBENZONE 60 mg/1 mL
INACTIVE INGREDIENTS: WATER; PROPYLENE GLYCOL; SILICON DIOXIDE; ALUMINUM STARCH OCTENYLSUCCINATE; DOCOSANOL; GLYCERYL MONOSTEARATE; MICROCRYSTALLINE CELLULOSE; BENZYL ALCOHOL; PALMITIC ACID; MYRISTYL ALCOHOL; STEARIC ACID; LAURYL ALCOHOL; CETYL ALCOHOL; ALOE VERA LEAF; CHAMOMILE; TOCOPHEROL; LECITHIN, SOYBEAN; CARBOXYMETHYLCELLULOSE SODIUM; CHLORPHENESIN; EDETATE DISODIUM; BUTYLENE GLYCOL

H.E.B Solutions Sunscreen Ultra SPF 50 Lotion

Active Ingredients

Acobenzone 2.0%, Homosalate 10.0%, Octisalate 5.0%, Octocrylene 7.0%, Oxybenzone 6.0%

Purpose

Sunscreen

Uses

- Helps prevent sunburn
- If used as directed with other sun protection measures (see Directions), decreases the risk of skin cancer and early skin aging caused by the sun

Warnings

For external use only

Do not use • on damaged or broken skin

When using this product keep out of eyes. Rinse with water to remove.

Stop use and ask doctor if • rash occurs

Keep out of reach of children. If swallowed, get medical help or contact a Poison Control Center right away.

Directions

- apply liberally 15 minutes before sun exposure
- reapply:

• after 80 minutes of swimming or sweating

• immediately after towel drying

• at least every 2 hours

- children under 6 months of age: ask a doctor
- Sun Protection Measures. Spending time in the sun increases your risk of skin cancer and early aging. To decrease this risk, regularly use a sunscreen with a broad-spectrum of 15 or higher and other sun protection measures including:

• limit time in the sun, especially from 10am-2pm

• wear long-sleeve shirts, pants, hats, and sunglasses.

Other Information

- protect this product from excessive heat and direct sun
- may stain or damage some fabrics, materials or surfaces

Inactive Ingredient(s)

water, propylene glycol, silica, aluminum starch octenylsuccinate, behenyl alcohol, butylated PVP, glyceryl stearate, microcrystalline cellulose, benzyl alcohol, palmitic acid, myristyl alcohol, stearic acid, saccharomyces/podophyllum peltatum ferment filtrate, lauryl alcohol, cetyl alcohol, aloe barbadensis leaf juice, chamomilla recutita (matricaria) flower extract, tocopherol (vitamin E), lecithin, cellulose gum, chlorphenesin, disodium EDTA, butylene glycol

Questions or Comments?

Call toll free 1-800-527-7731

PACKAGE LABEL

H.E.B Solutions Sunscreen Ultra SPF 50 Lotion

3 FL OZ (89mL)

NDC 37808-956-09

H.E.B Solutions Sunscreen Ultra SPF 50 Lotion

8 FL OZ (237mL)

NDC 37808-956-12